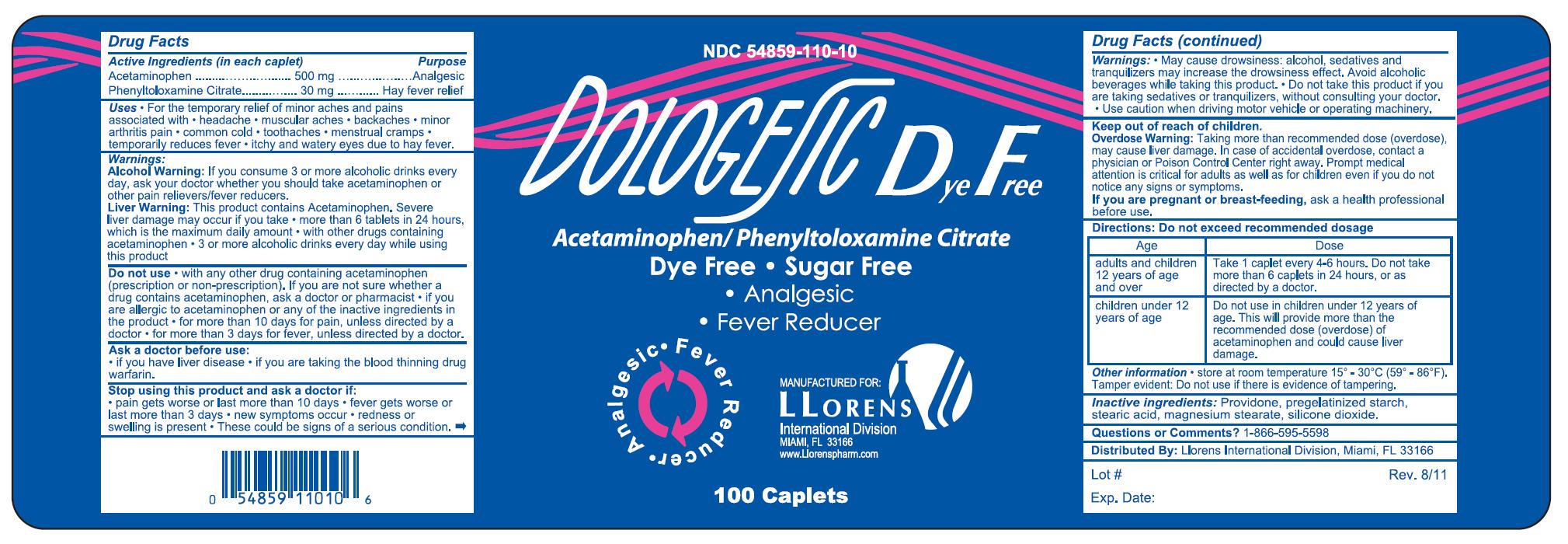 DRUG LABEL: Dologesic
NDC: 54859-110 | Form: TABLET
Manufacturer: LLORENS PHARMACEUTICALS INTERNATIONAL DIVISION
Category: otc | Type: HUMAN OTC DRUG LABEL
Date: 20120410

ACTIVE INGREDIENTS: ACETAMINOPHEN 500 mg/1 1; PHENYLTOLOXAMINE CITRATE 30 mg/1 1
INACTIVE INGREDIENTS: POVIDONE; STARCH, CORN; STEARIC ACID; MAGNESIUM STEARATE; SILICON DIOXIDE

Drug Facts

Active Ingredients (in each caplet) Purpose

Acetaminophen ............................. 500 mg .......... Analgesic

Phenyltoloxamine Citrate ............... 30 mg ............ Hay fever relief

Uses

- For the temporary relief of minor aches and pains associated with
- headache
- muscular aches
- backaches
- minor arthritis pain
- common cold
- toothaches
- menstrual cramps
- temporarily reduces fever
- itchy and watery eyes due to hay fever

Warnings

Alcohol Warning:If you consume 3 or more alcoholic drinks every day, ask your doctor whether you should take acetaminophen or other pain relievers/fever reducers/

Liver Warning: This product contains Acetaminophen, Sever liver damage may occur if you take

- more than 6 tablets in 24 hours,which is the maximum daily amount
- with other drugs containing acetaminophen
- 3 or more alcoholic drinks every day while using this product

Do not use

- with any other drug containing acetaminophen (prescription or non-prescription).
  If you are not sure whether a drug contains acetaminophen, ask a doctor or pharmacist
- if you are allergic to acetaminophen or any of the inactive ingredients in the product
- for more than 10 days for pain, unless directed by a doctor
- for more than 3 days for fever, unless directed by a doctor

Ask a doctor before use:

- if you have liver disease
- if you are taking the thinning drug warfarin

Stop using this product and ask doctor if:

- pain gets worse or lasts more than 10 days
- fever gets worse or lasts more than 3 days
- new symptoms occur
- redness or swelling is present
- These could be signs of a serious condition.

Warnings:

- May cause drowsiness: alcohol, sedatives and tranquilizers may increase the drowsiness effect. Avoid alcoholic beverages while taking this product
- Do not take this product if you are taking sedatives or tranquilizers without consulting a doctor
- Use caution when driving motor vehicles or operating machinery

Keep out of reach of children.

PREGNANCY OR BREAST FEEDING

If you are pregnant or breast-feeding, ask a health professional before use.

Directions: Do not exceed recommended dosage

AGE | Dose
adults and children 12 years of age and over | take 1 tablet every 4-6 hours. Do not take more than 6 tablets in 24 hours, or as directed by a doctor
children under 12 years of age | Do not use in children under 12 years of age. This will provide more than the recommended dose (overdose) of acetaminophen and could cause liver damage

INDICATIONS AND USAGE

Overdose Warning:Taking more than the recommended dose (overdose), may cause liver damage. In case of accidental overdose, contact a physician or Poison Control Center right away. Prompt medical attention is critical for adults as well as for children even if you do not notice any signs or symptoms.

Other information:Store at room temperature 15-30 degrees C (59-86 degrees F).

Tamper Evident: Do not use if there is evidence of tampering.

INACTIVE INGREDIENT

Inactive Ingredients: Povidone, pregelatinized starch, stearic acid, magnesium stearate, silicon dioxide.

Questions or Comments?1-866-595-5598